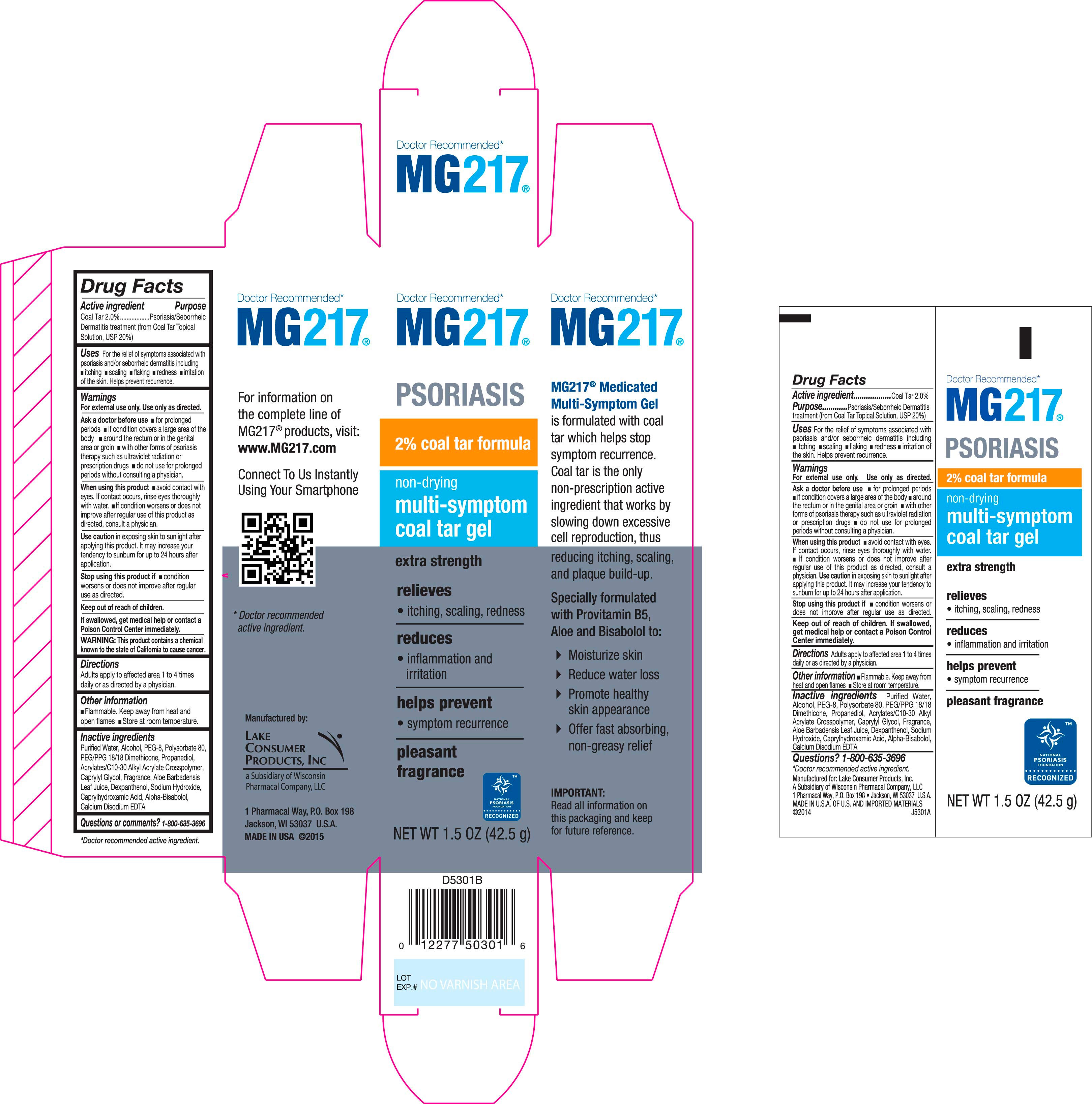 DRUG LABEL: MG217 Psoriasis
NDC: 68093-7226 | Form: GEL
Manufacturer: Wisconsin Pharmacal Company
Category: otc | Type: HUMAN OTC DRUG LABEL
Date: 20151106

ACTIVE INGREDIENTS: COAL TAR 0.02 g/1 g
INACTIVE INGREDIENTS: WATER; SODIUM HYDROXIDE; POLYETHYLENE GLYCOL 400; PEG/PPG-18/18 DIMETHICONE; CAPRYLYL GLYCOL; CARBOMER INTERPOLYMER TYPE A (55000 MPA.S); DEXPANTHENOL; PROPANEDIOL; CAPRYLHYDROXAMIC ACID; EDETATE CALCIUM DISODIUM; POLYSORBATE 80; .ALPHA.-BISABOLOL, (+)-; ALOE VERA LEAF

Drug Facts

Active Ingredient

Coal Tar 2%

Purpose

Psoriasis, Seborrheic Dermatitis, Dandruff Treatment (from Coal Tar Topical Solution, USP 20%)

Uses

For the temporary relief of these symptoms associated with psoriasis and/or seborrheic dermatitis including,

- itching
- scaling
- flaking
- redness
- irritation of the scalp

Helps prevent recurrence.

Warnings

For external use only. Use only as directed.

Ask doctor before use

- for prolonged periods
- if condition covers a large area of the body.
- around the rectum or in the genital area or groin
- with other forms of psoriasis therapy such as ultraviolet radiation or prescription drugs
- do not use for prolonged periods without consulting a physician

When using this product

- avoid contact with the eyes. If contact occurs, rinse eyes thoroughly with water.
- If condition worsens or does not improve after regular use of this product as directed, consult a physician.
- Use caution in exposing skin to sunlight. It may increase your tendency to sunburn for up to 24 hours after application

Stop use and ask a doctor if

- condition worsens or does not improve after regular use of this product as directed.

Keep out of reach of children.

OTHER SAFETY INFORMATION

If swallowed, get medical help or contact a Poison Control Center immediately. This product contains coal tar, a product known in the state of California to cause cancer.

Flamable. Keep away from heat and open flames. Store at room temperature.

Inactive ingredients

Purified Water, Alcohol, PEG-8, Polysorbate 80, PEG/PPG 18/18 Dimethicone, Propanediol, Acrylates/C10-30 Alkyl Acrylate Crosspolymer, Caprylyl Glycol, Fragrance, Aloe Barbadensis Leaf Juice, Dexpanthenol, Sodium Hydroxide, Caprylhdroxamic Acid, Alpha-Bisabolol, Calcium Disodium EDTA

Directions

Adults aply to affected area 1 to 4 times daily or as directed by a physician.

Questions?

1-800-635-3696

Carton and Label